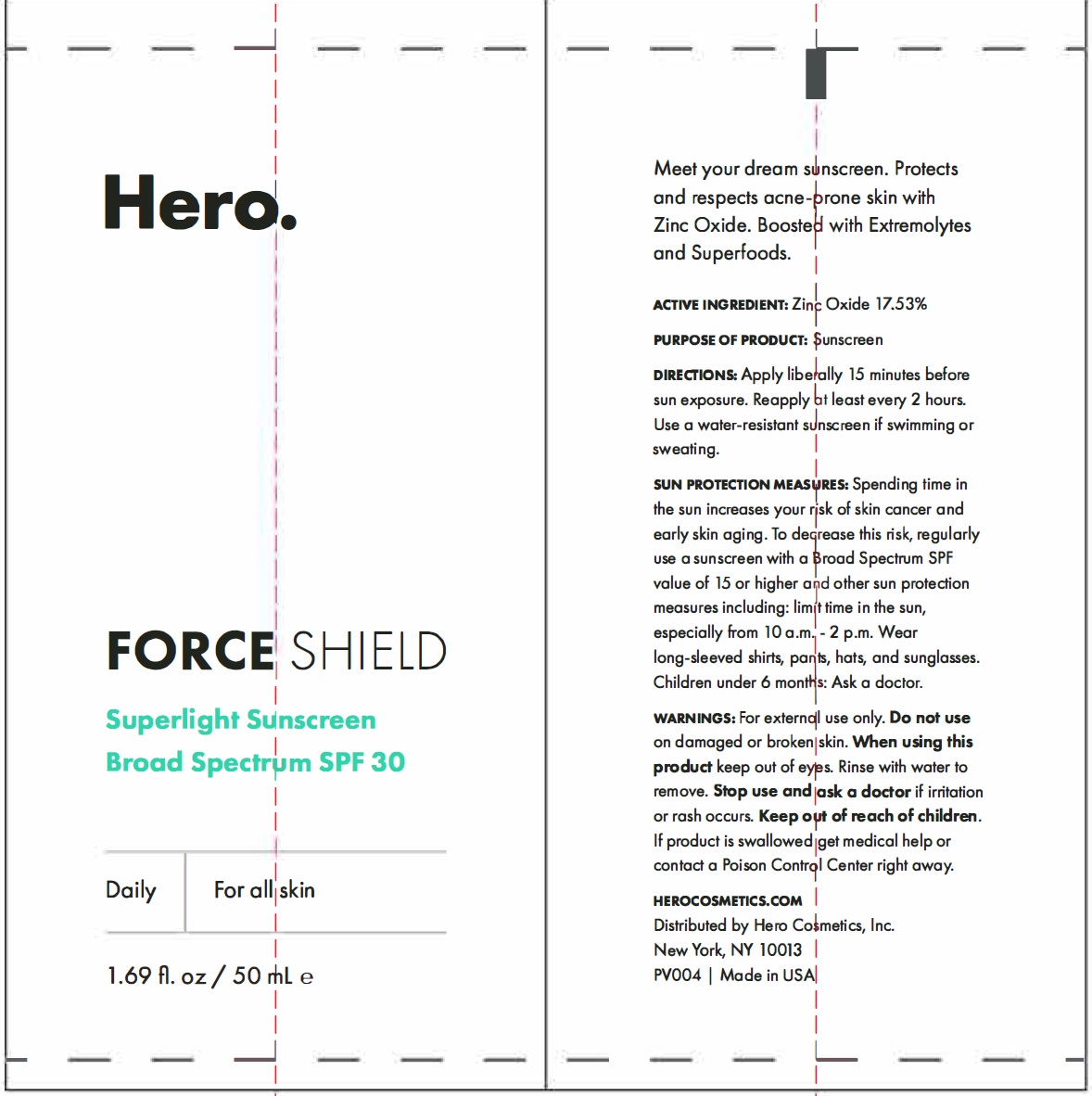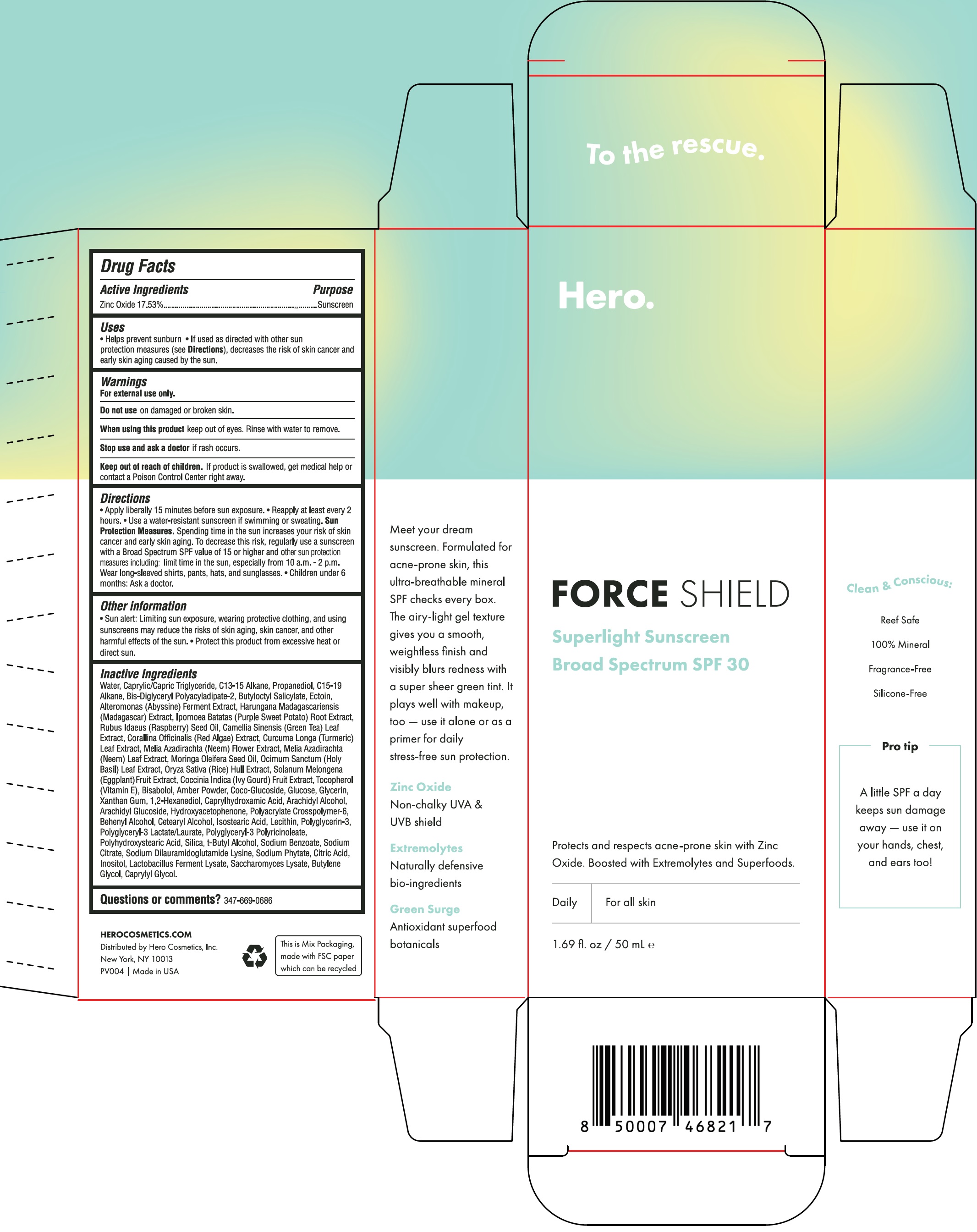 DRUG LABEL: Hero Force Shield SPF 30
NDC: 73381-505 | Form: CREAM
Manufacturer: Hero Cosmetics, Inc.
Category: otc | Type: HUMAN OTC DRUG LABEL
Date: 20250102

ACTIVE INGREDIENTS: ZINC OXIDE 175.3 mg/1 mL
INACTIVE INGREDIENTS: WATER; MEDIUM-CHAIN TRIGLYCERIDES; C13-15 ALKANE; PROPANEDIOL; C15-19 ALKANE; BIS-DIGLYCERYL POLYACYLADIPATE-2; BUTYLOCTYL SALICYLATE; ECTOINE; ALTEROMONAS MACLEODII POLYSACCHARIDES; SWEET POTATO; RASPBERRY SEED OIL; GREEN TEA LEAF; CORALLINA OFFICINALIS; CURCUMA LONGA LEAF; AZADIRACHTA INDICA FLOWER; AZADIRACHTA INDICA LEAF; MORINGA OLEIFERA SEED OIL; HOLY BASIL LEAF; RICE BRAN; EGGPLANT; COCCINIA GRANDIS FRUIT; TOCOPHEROL; LEVOMENOL; AMBER; COCO GLUCOSIDE; ANHYDROUS DEXTROSE; GLYCERIN; XANTHAN GUM; 1,2-HEXANEDIOL; CAPRYLHYDROXAMIC ACID; ARACHIDYL ALCOHOL; ARACHIDYL GLUCOSIDE; HYDROXYACETOPHENONE; AMMONIUM ACRYLOYLDIMETHYLTAURATE, DIMETHYLACRYLAMIDE, LAURYL METHACRYLATE AND LAURETH-4 METHACRYLATE COPOLYMER, TRIMETHYLOLPROPANE TRIACRYLATE CROSSLINKED (45000 MPA.S); DOCOSANOL; CETOSTEARYL ALCOHOL; ISOSTEARIC ACID; POLYGLYCERIN-3; POLYGLYCERYL-3 LAURATE; POLYGLYCERYL-3 PENTARICINOLEATE; POLYHYDROXYSTEARIC ACID (2300 MW); SILICON DIOXIDE; TERT-BUTYL ALCOHOL; SODIUM BENZOATE; SODIUM CITRATE; SODIUM DILAURAMIDOGLUTAMIDE LYSINE; PHYTATE SODIUM; CITRIC ACID MONOHYDRATE; INOSITOL; SACCHAROMYCES LYSATE; BUTYLENE GLYCOL; CAPRYLYL GLYCOL

Hero Force Shield SPF 30

Active Ingredients

Zinc Oxide 17.53%

Purpose

Sunscreen

Uses

- Helps prevent sunburn
- If used as directed with other sun protection measures (see), decreases the risk of skin cancer and early skin aging caused by the sun. Directions

Warnings

For external use only.

Do not use

on damaged or broken skin.

When using this product

keep out of eyes. Rinse with water to remove.

Stop use and ask a doctor if

rash occurs.

Keep out of reach of children.

If product is swallowed, get medical help or contact a Poison Control Center right away.

Directions

- Apply liberally 15 minutes before sun exposure.
- Reapply at least every 2 hours.
- Use a water-resistant sunscreen if swimming or sweating.

- Children under 6 months of age: Ask a doctor.

Spending time in the sun increases your risk of skin cancer and early skin aging. To decrease this risk, regularly use a sunscreen with a Broad Spectrum SPF value of 15 or higher and other sun protection measures including: limit time in the sun, especially from 10 a.m. - 2 p.m., Wear long-sleeved shirt, pants, hats and sunglasses. Sun Protection Measures:

Other information

- Sun alert: Limiting sun exposure, wearing protective clothing, and using sunscreens may reduce the risks of skin aging, skin cancer, and other harmful effects of the sun.
- Protect this product from excessive heat or direct sun.

Inactive Ingredients

Water, Caprylic/Capric Triglyceride, C13-15 Alkane, Propanediol, C15-19 Alkane, Bis-Diglyceryl Polyacyladipate-2, Butyloctyl Salicylate, Ectoin, Alteromonas (Abyssine) Ferment Extract, Harungana Madagascariensis (Madagascar) Extract, Ipomoea Batatas (Purple Sweet Potato) Root Extract, Rubus Idaeus (Raspberry) Seed Oil, Camellia Sinesis (Green Tea) Leaf Extract, Corallina Officinalis (Red Algae) Extract, Curcuma Longa (Turmeric) Leaf Extract, Melia Azadirachta (Neem) Flower Extract, Melia Azadirachta (Neem) Leaf Extract, Moringa Oleifera Seed Oil, Ocimum Sanctum (Holy Basil) Leaf Extract, Oryza Sativa (Rice) Hull Extract, Solanum Melongena (Eggplant) Fruit Extract, Coccinia Indica (Ivy Gourd) Fruit Extract, Tocopherol (Vitamin E), Bisabolol, Amber Powder, Coco-Glucoside, Glucose, Glycerin, Xanthan Gum, 1,2-Hexanediol, Caprylhydroxamic Acid, Arachidyl Alcohol, Arachidyl Glucoside, Hydroxyacetophenone, Polyacrylate Crosspolymer-6, Behenyl Alcohol, Cetearyl Alcohol, Isostearic Acid, Lecithin, Polyglycerin-3, Polyglyceryl-3 Lactate/Laurate, Polyglyceryl-3 Polyricinoleate, Polyhydroxystearic Acid, Silica, t-Butyl Alcohol, Sodium Benzoate, Sodium Citrate, Sodium Dilauramidoglutamide Lysine, Sodium Phytate, Citric Acid, Inositol, Lactobacillus Ferment Lysate, Saccharomyces Lysate, Butylene Glycol, Caprylyl Glycol.

Questions or comments?

347-669-0686